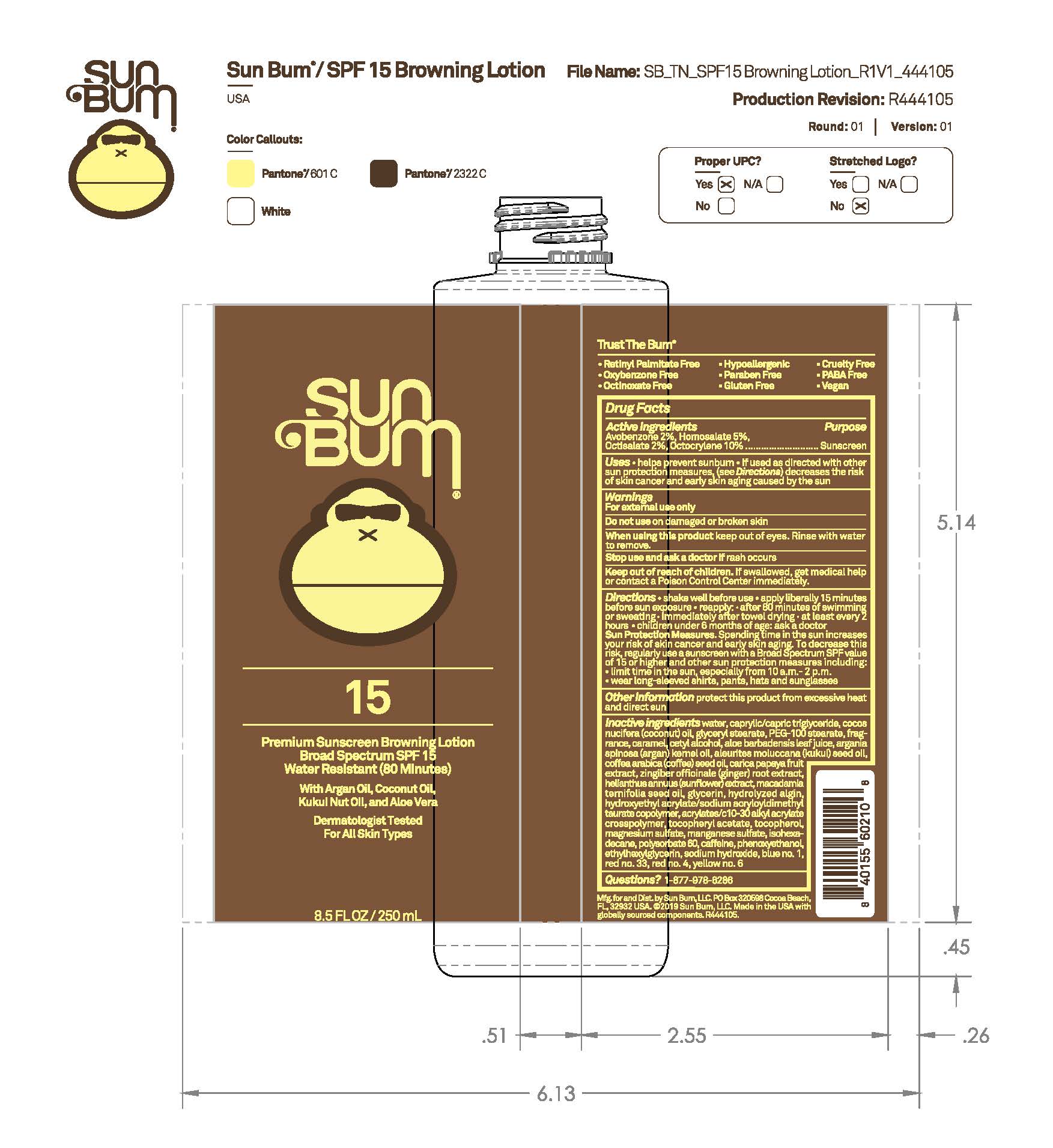 DRUG LABEL: Sun Bum 15 Premium Sunscreen Browning
NDC: 69039-801 | Form: LOTION
Manufacturer: Sun Bum, LLC
Category: otc | Type: HUMAN OTC DRUG LABEL
Date: 20250814

ACTIVE INGREDIENTS: HOMOSALATE 50 mg/1 mL; AVOBENZONE 20 mg/1 mL; OCTISALATE 20 mg/1 mL; OCTOCRYLENE 100 mg/1 mL
INACTIVE INGREDIENTS: CAPRYLIC/CAPRIC TRIGLYCERIDE; ARGAN OIL; KUKUI NUT OIL; COFFEA ARABICA (COFFEE) SEED OIL; TOCOPHEROL; PHENOXYETHANOL; HYDROXYETHYL ACRYLATE/SODIUM ACRYLOYLDIMETHYL TAURATE COPOLYMER (45000 MPA.S AT 1%); MANGANESE SULFATE; ISOHEXADECANE; POLYSORBATE 60; CETYL ALCOHOL; BLUE 1; YELLOW 6; MACADAMIA TERNIFOLIA SEED OIL; RED 4; GLYCERYL STEARATE; HELIANTHUS ANNUUS FLOWERING TOP; CARAMEL; ETHYLHEXYLGLYCERIN; .ALPHA.-TOCOPHEROL ACETATE; MAGNESIUM SULFATE; SODIUM HYDROXIDE; PEG-100 STEARATE; CARICA PAPAYA (PAPAYA) FRUIT; GLYCERIN; LAMINARIA DIGITATA HYDROLYZED ALGINIC ACID; RED 33; WATER; COCOS NUCIFERA (COCONUT) OIL; ALOE BARBADENSIS LEAF JUICE; ACRYLATES/C10-30 ALKYL ACRYLATE CROSSPOLYMER (60000 MPA.S); CAFFEINE; GINGER

Sun Bum 15 Premium Sunscreen Browning

Active Ingredients

Homosalate: 5%
Octocrylene: 10%
Octisalate: 2%
Avobenzone 2%

Purpose

Sunscreen

Uses

• helps prevent sunburn • if used as directed with other sun protection measures, (see Directions) decreases the risk of skin cancer and early skin aging caused by the sun

Warnings

For external use only

Do not use on damaged or broken skin

When using this product keep out of eyes. Rinse with water to remove.

Stop use and ask a doctor if rash occurs

Keep out of reach of children. If swallowed, get medical help or contact a Poison Control Center immediately.

Warnings

Keep Out Of Reach Of Children

Directions

• shake well before use

• apply liberally 15 minutes before sun exposure

• reapply: • after 80 minutes of swimming or sweating • immediately after towel drying • at least every 2 hours

• children under 6 months of age: ask a doctor

• Sun Protection Measures. Spending time in the sun increases your risk of skin cancer and early skin aging. To decrease this risk, regularly use a sunscreen with a Broad Spectrum SPF value of 15 or higher and other sun protection measures including:

• limit time in the sun, especially from 10 a.m.- 2 p.m.

• wear long-sleeved shirts, pants, hats and sunglasses

Directions

• shake well before use

• apply liberally 15 minutes before sun exposure

Other Information

protect this product from excessive heat and direct sun

Inactive Ingredients

water, caprylic/capric triglyceride, cocos nucifera (coconut) oil, glyceryl stearate, PEG-100 stearate, fragrance, caramel, cetyl alcohol, aloe barbadensis leaf juice, argania spinosa (argan) kernel oil, aleurites moluccana (kukui) seed oil, coffea arabica (coffee) seed oil, carica papaya fruit extract, zingiber officinale (ginger) root extract, helianthus annuus (sunflower) extract, macadamia ternifolia seed oil, glycerin, hydrolyzed algin, hydroxyethyl acrylate/sodium acryloyldimethyl taurate copolymer, acrylates/c10-30 alkyl acrylate crosspolymer, tocopheryl acetate, tocopherol, magnesium sulfate, manganese sulfate, isohexadecane, polysorbate 60, caffeine, phenoxyethanol, ethylhexylglycerin, sodium hydroxide, blue no. 1, red no. 33, red no. 4, yellow no. 6

Questions?

1-877-978-6286